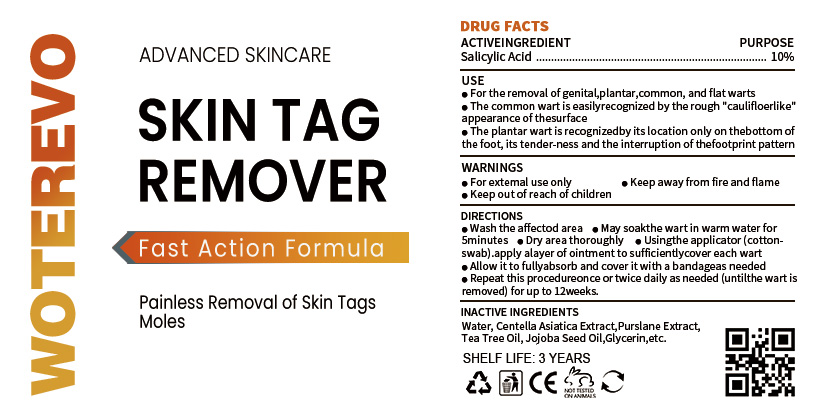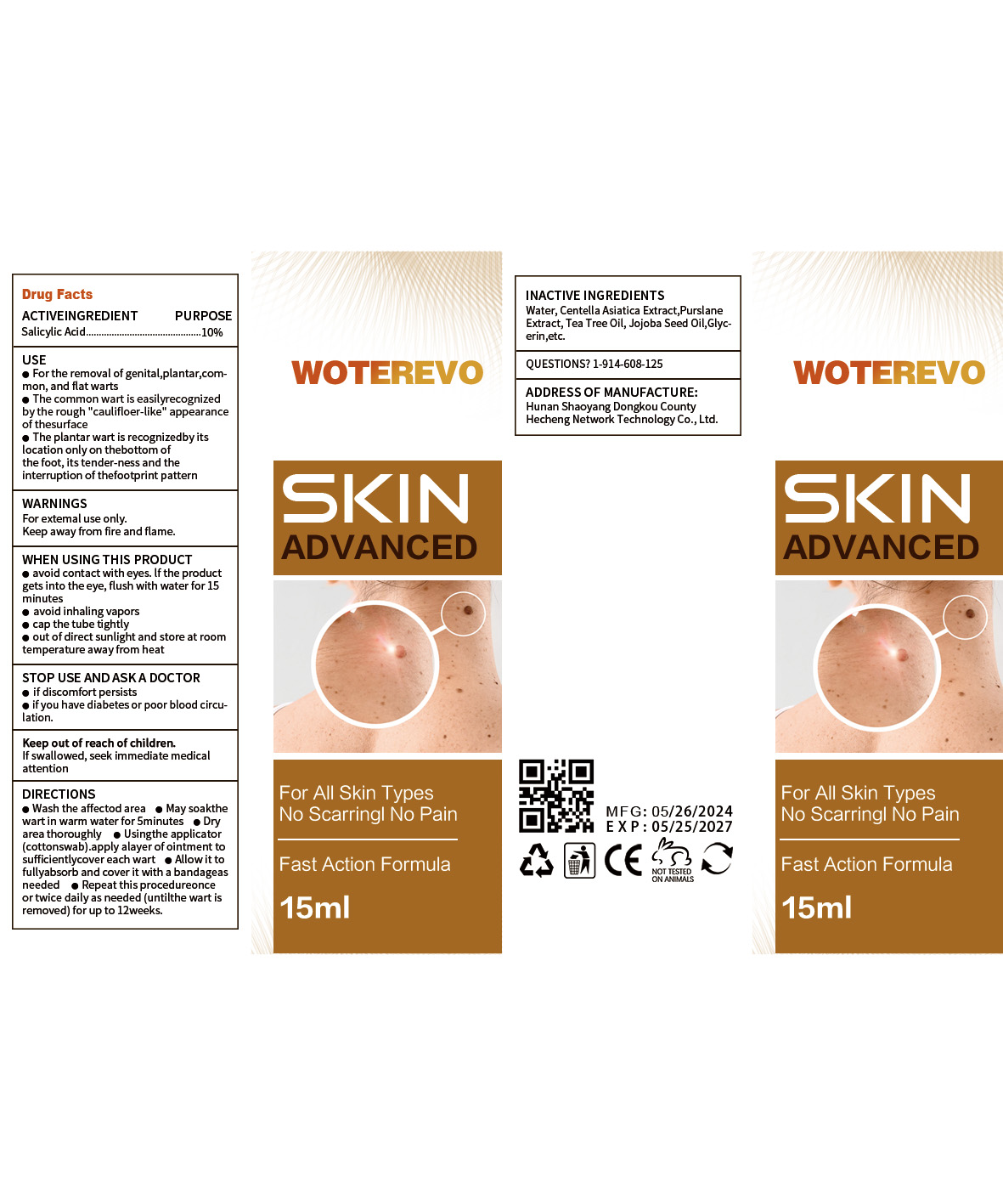 DRUG LABEL: Skin Tag Remover
NDC: 84288-003 | Form: LIQUID
Manufacturer: Dongkou County Hecheng Network Technology Co., Ltd.
Category: otc | Type: HUMAN OTC DRUG LABEL
Date: 20240618

ACTIVE INGREDIENTS: SALICYLIC ACID 10 g/100 mL
INACTIVE INGREDIENTS: GLYCERIN; WATER; TEA TREE OIL; JOJOBA OIL; PORTULACA OLERACEA WHOLE; CENTELLA ASIATICA TRITERPENOIDS

Skin Tag Remover

ACTIVE INGREDIENT

SALICYLIC ACID 10%

PURPOSE

For the removal of genital,plantar,common, and flat warts.The common wart is easilyrecog-nized by the rough "cauli-flow-er-like" appearance of thesurface.The plantar wart is recognizedby itslocation only on thebottom of thefoot, its tender-ness and the inter-ruption of thefootprint pattern.

Keep out of reach of children.

INDICATIONS AND USAGE

For the removal of genital,plantar,common, and flat warts.The common wart is easilyrecog-nized by the rough "cauli-flow-er-like" appearance of thesurface.The plantar wart is recognizedby itslocation only on thebottom of thefoot, its tender-ness and the inter-ruption of thefootprint pattern.

WARNINGS

For extemal use only.

Keep away from fire and flame

DOSAGE AND ADMINISTRATION

Wash the affectod area Maysoakthe wart in warm water for5minutes Dry area thoroughlyUsingthe applicator (cottonswab).apply alayer of ointment to suffi-cientlycover each wart.Allow it to fullyabsorb and cover itwith a bandageas needed Repeat.this procedureonce or twicedaily as needed (untilthe wart isremoved) for up to 12weeks

INACTIVE INGREDIENT

Water
Centella Asiatica Extract
Purs-lane Extract
Tea Tree Oil
Jojoba Seed Oil
Glycerin